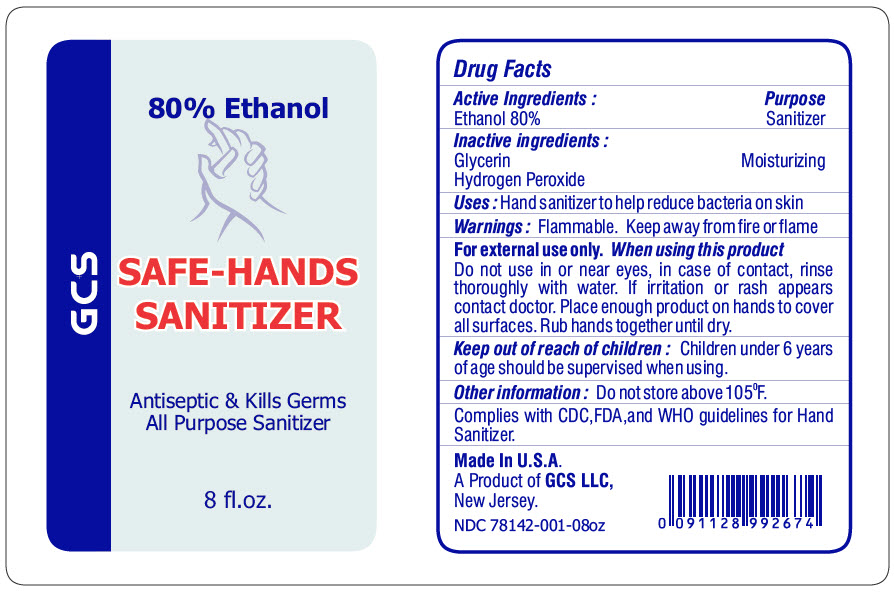 DRUG LABEL: SAFE-HANDS SANITIZER
NDC: 78142-001 | Form: LIQUID
Manufacturer: GLOBAL COMMODITY SUPPLIER LLC
Category: otc | Type: HUMAN OTC DRUG LABEL
Date: 20200714

ACTIVE INGREDIENTS: Alcohol 80 mL/100 mL
INACTIVE INGREDIENTS: GLYCERIN; HYDROGEN PEROXIDE

SAFE-HANDS SANITIZER

Drug Facts

ACTIVE INGREDIENT

PURPOSE

INACTIVE INGREDIENT

Active Ingredients : | Purpose
Ethanol 80% | Sanitizer
Inactive ingredients :
Glycerin | Moisturizing
Hydrogen Peroxide

Uses

Hand sanitizer to help reduce bacteria on skin

Warnings

Flammable. Keep away from fire or flame

For external use only.

When using this product

Do not use in or near eyes, in case of contact, rinse thoroughly with water. If irritation or rash appears contact doctor.

DOSAGE AND ADMINISTRATION

Place enough product on hands to cover all surfaces. Rub hands together until dry.

Keep out of reach of children

Children under 6 years of age should be supervised when using.

Other information

Do not store above 105°F.

Complies with CDC,FDA,and WHO guidelines for Hand Sanitizer.

Made In U.S.A.
A Product of GCS LLC,
New Jersey.

NDC 78142-001-08oz

PRINCIPAL DISPLAY PANEL - 8 fl.oz. Bottle Label

80% Ethanol

GCS

SAFE-HANDS
SANITIZER

Antiseptic & Kills Germs
All Purpose Sanitizer

8 fl.oz.